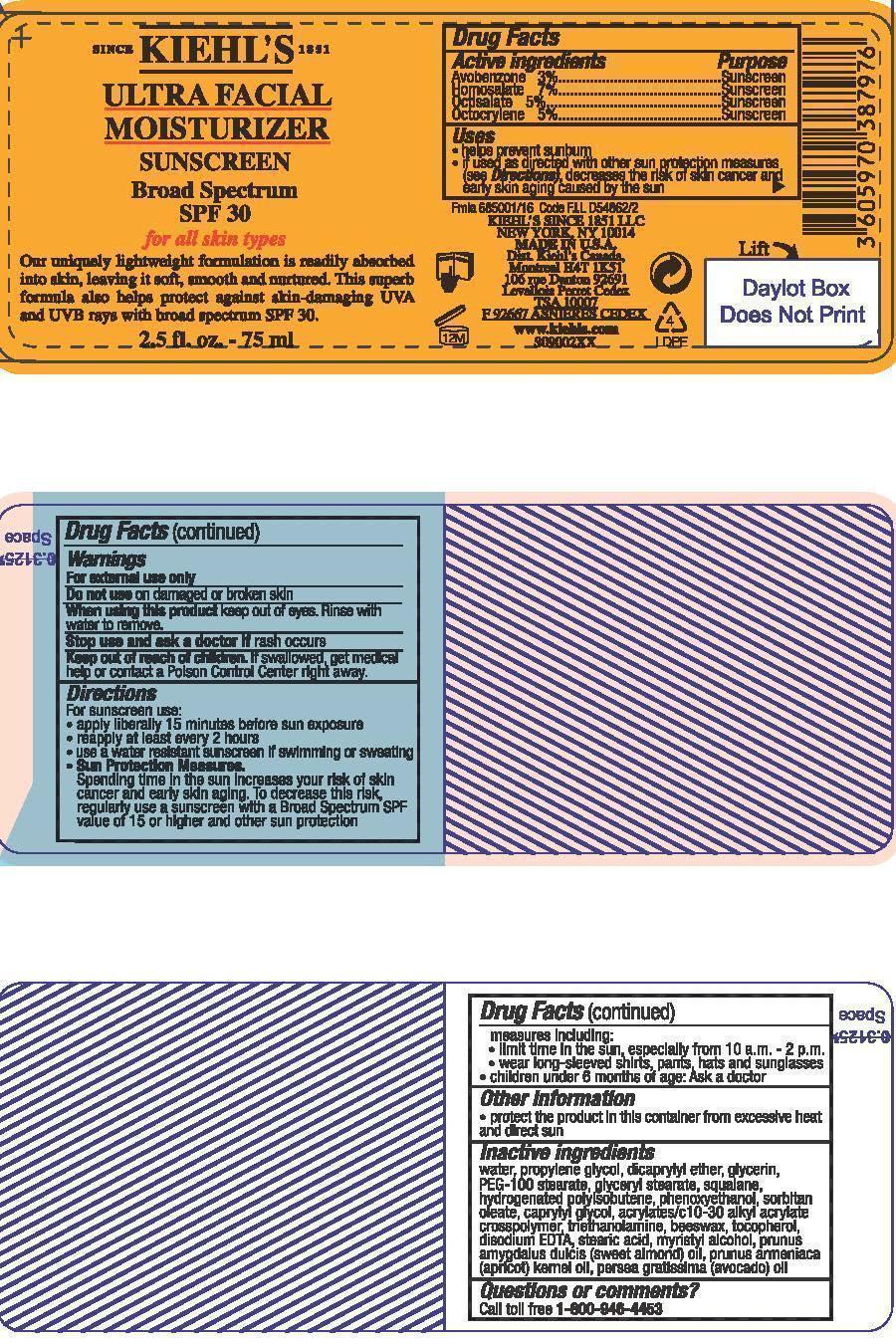 DRUG LABEL: Kiehls Since 1851 Ultra Facial Moisturizer Broad Spectrum SPF 30 Sunscreen For All Skin Types
NDC: 49967-797 | Form: LOTION
Manufacturer: L'Oreal USA Products Inc
Category: otc | Type: HUMAN OTC DRUG LABEL
Date: 20231230

ACTIVE INGREDIENTS: AVOBENZONE 30 mg/1 mL; HOMOSALATE 70 mg/1 mL; OCTISALATE 50 mg/1 mL; OCTOCRYLENE 50 mg/1 mL
INACTIVE INGREDIENTS: WATER; PROPYLENE GLYCOL; DICAPRYLYL ETHER; GLYCERIN; PEG-100 STEARATE; GLYCERYL MONOSTEARATE; SQUALANE; PHENOXYETHANOL; CAPRYLYL GLYCOL; TOCOPHEROL; EDETATE DISODIUM; STEARIC ACID; MYRISTYL ALCOHOL; ALMOND OIL; APRICOT KERNEL OIL; AVOCADO OIL

Drug Facts

Active ingredients

Avobenzone 3%

Homosalate 7%

Octisalate 5%

Octocrylene 5%

Purpose

Sunscreen

Uses

- helps prevent sunburn

- if used as directed with other sun protection measures (see Directions), decreases the risk of skin cancer and early skin aging caused by the sun

Warnings

For external use only

Do not use

on damaged or broken skin

When using this product

keep out of eyes. Rinse with water to remove.

Stop use and ask a doctor if

rash occurs

Keep out of reach of children.

If swallowed, get medical help or contact a Poison Control Center right away.

Directions

For sunscreen use:

● apply liberally 15 minutes before sun exposure

● reapply at least every 2 hours

● use a water resistant sunscreen if swimming or sweating

● Sun Protection Measures. Spending time in the sun increases your risk of skin cancer and early skin aging. To decrease this risk, regularly use a sunscreen with a Broad Spectrum SPF value of 15 or higher and other sun protection measures including:

● limit time in the sun, especially from 10 a.m. – 2 p.m.

● wear long-sleeved shirts, pants, hats, and sunglasses

● children under 6 months of age: Ask a doctor

Other information

protect the product in this container from excessive heat and direct sun

Inactive ingredients

water, propylene glycol, dicaprylyl ether, glycerin, PEG-100 stearate, glyceryl stearate, squalane, hydrogenated polyisobutene, phenoxyethanol, sorbitan oleate, caprylyl glycol, acrylates/c10-30 alkyl acrylate crosspolymer, triethanolamine, beeswax, tocopherol, disodium EDTA, stearic acid, myristyl alcohol, prunus amygdalus dulcis (sweet almond) oil, prunus armeniaca (apricol) kernel oil, persea gratissima (avocado) oil

Questions or comments?

Call toll free 1-800-946-4453